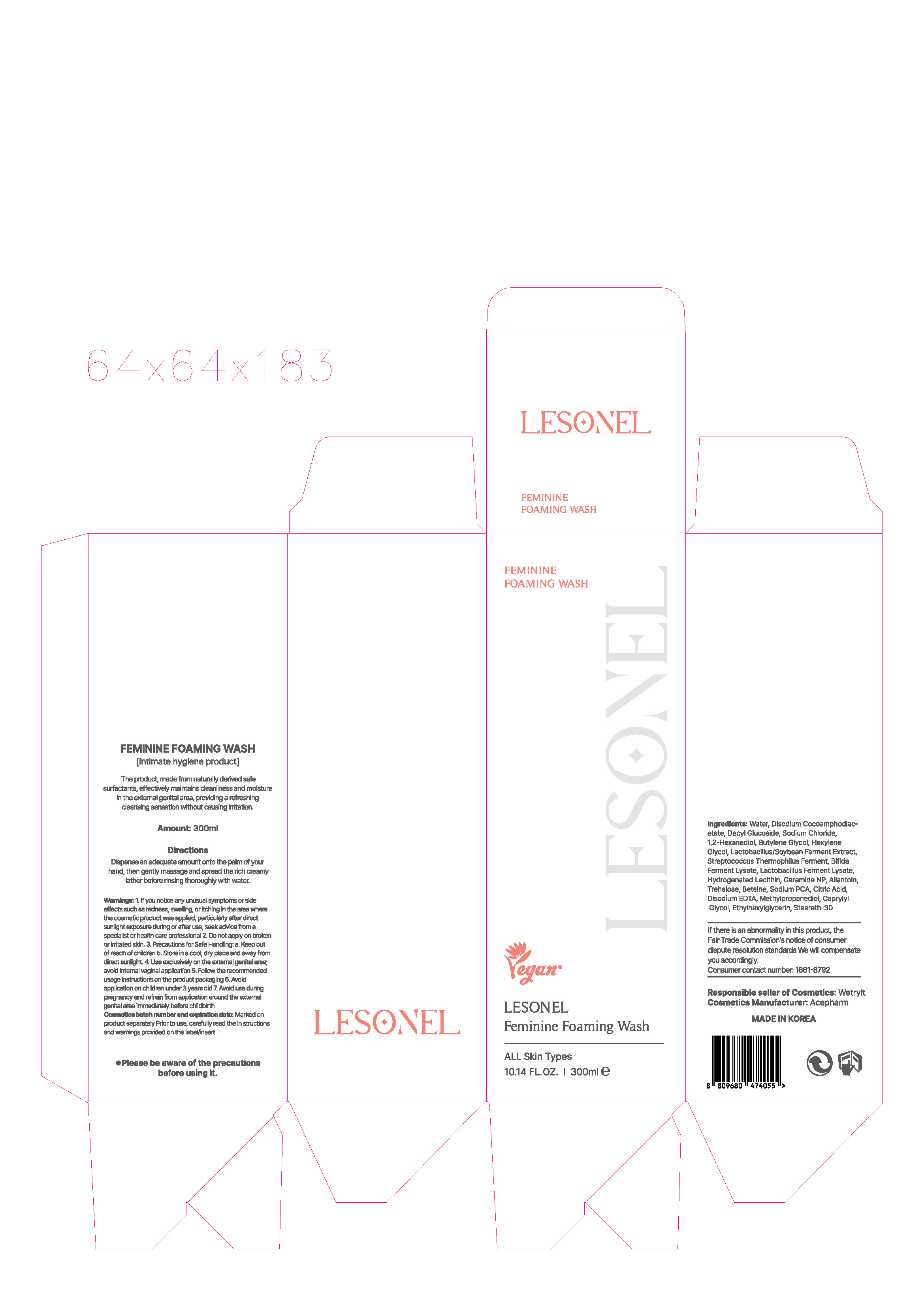 DRUG LABEL: LESONEL FEMININE FOAMING WASH
NDC: 74196-0011 | Form: LIQUID
Manufacturer: ACE PHARMACEUTICAL CO.,LTD.
Category: otc | Type: HUMAN OTC DRUG LABEL
Date: 20250313

ACTIVE INGREDIENTS: ALLANTOIN 0.1 g/100 mL
INACTIVE INGREDIENTS: WATER; BUTYLENE GLYCOL

Drug Facts

ACTIVE INGREDIENT

ALLANTOIN

INACTIVE INGREDIENT

Water
Disodium Cocoamphodiacetate
Sodium Chloride
1,2-Hexanediol

Decyl Glucoside
Butylene Glycol
Hexylene Glycol
Lactobacillus/Soybean Ferment Extract
Streptococcus Thermophilus Ferment
Bifida Ferment Lysate

Lactobacillus Ferment Lysate
Hydrogenated Lecithin

Ceramide NP
Allantoin
Trehalose
Betaine
Sodium PCA
Citric Acid
Disodium EDTA

Methylpropanediol
Caprylyl Glycol
Ethylhexylglycerin
Steareth-30

PURPOSE

The product, made from naturally derived safe surfactants, effectively maintains cleanliness and moisture

in the external genital area, providing a refreshing cleansing sensation without causing irritation.

KEEP OUT OF REACH OF THE CHILDREN

INDICATIONS AND USAGE

Dispense an adequate amount onto the palm of your hand, then gently massage and spread the rich creamy

lather before rinsing thoroughly with water.

WARNINGS

Warnings: 1. If you notice any unusual symptoms or side effects such as redness, swelling, or itching in the area where the cosmetic product was applied, particularly after direct sunlight exposure during or after use, seek advice from a specialist or health care professional 2. Do not apply on broken or irritated skin. 3. Precautions for Safe Handling: a. Keep out of reach of children b. Store in a cool, dry place and away from direct sunlight. 4. Use exclusively on the external genital area; avoid internal vaginal application 5. Follow the recommended usage instructions on the product packaging 6. Avoid application on children under 3 years old 7. Avoid use during pregnancy and refrain from application around the external genital area immediately before childbirthPrecautions for Safe Handling: a. Keep out of reach of children

DOSAGE AND ADMINISTRATION

for vaginal use only